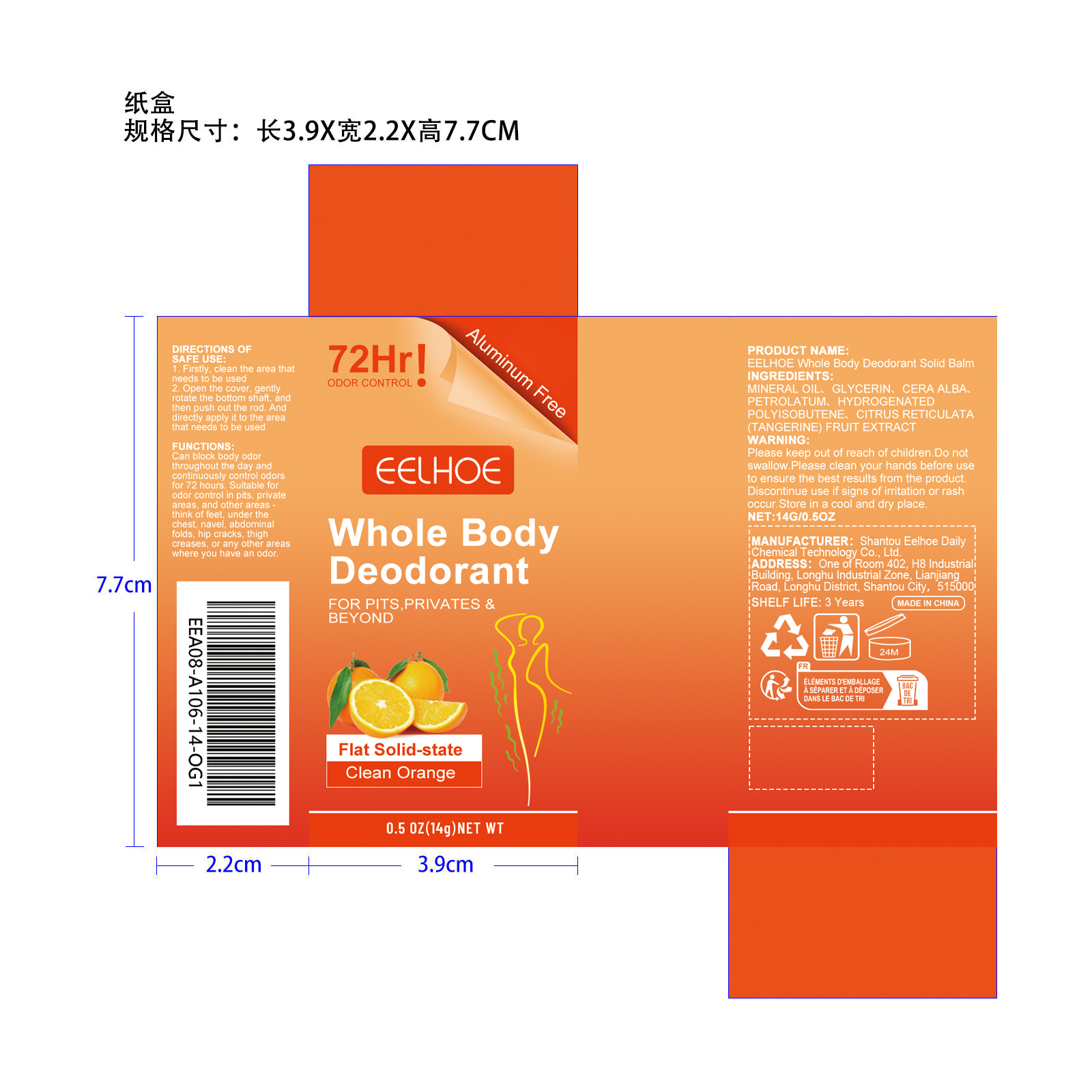 DRUG LABEL: EELHOE Whole Body Deodorant Solid Balm
NDC: 85064-025 | Form: CREAM
Manufacturer: Shantou Eelhoe Daily Chemical Technology Co., Ltd.
Category: otc | Type: HUMAN OTC DRUG LABEL
Date: 20251207

ACTIVE INGREDIENTS: CITRUS RETICULATA FRUIT OIL 0.028 mg/14 mg
INACTIVE INGREDIENTS: MINERAL OIL 7.252 mg/14 mg; PETROLATUM 3.5 mg/14 mg; HYDROGENATED POLYISOBUTENE 8 0.7 mg/14 mg; CARYA ALBA BARK 1.4 mg/14 mg; GLYCERIN 1.12 mg/14 mg

ACTIVE INGREDIENT

CITRUS RETICULATA (TANGERINE) FRUIT EXTRACT

PURPOSE

Can block body odor throughout the day and continuously control odors for 72 hours. Suitable for odor control in pits, private areas, and other areasthink of feet, under the chest, navel, abdominal folds, hip cracks, thigh creases, or any other areas where you have an odor.

WHEN USING

1. Firstly, clean the area that needs to be used 2. Open the cover, gently rotate the bottom shaft, and then push out the rod. And directly apply it to the area that needs to be used

WARNINGS

Please keep out of reach of children. Do not swallow.Please clean your hands before use to ensure the best results from the product. Discontinue use if signs of irritation or rash occur. Store in a cool and dry place.

DO NOT USE

Discontinue use if signs of irritation or rash occur.

STOP USE

Discontinue use if signs of irritation or rash occur.

KEEP OUT OF REACH OF CHILDREN

Please keep out of reach of children. Do not swallow.

STORAGE AND HANDLING

Store in a cool and dry place.

DOSAGE AND ADMINISTRATION

1. Firstly, clean the area that needs to be used 2. Open the cover, gently rotate the bottom shaft, and then push out the rod. And directly apply it to the area that needs to be used

INDICATIONS AND USAGE

1. Firstly, clean the area that needs to be used 2. Open the cover, gently rotate the bottom shaft, and then push out the rod. And directly apply it to the area that needs to be used

INACTIVE INGREDIENT

MINERAL OIL、 GLYCERIN、 CERA ALBA、 PETROLATUM、 HYDROGENATED POLYISOBUTENE